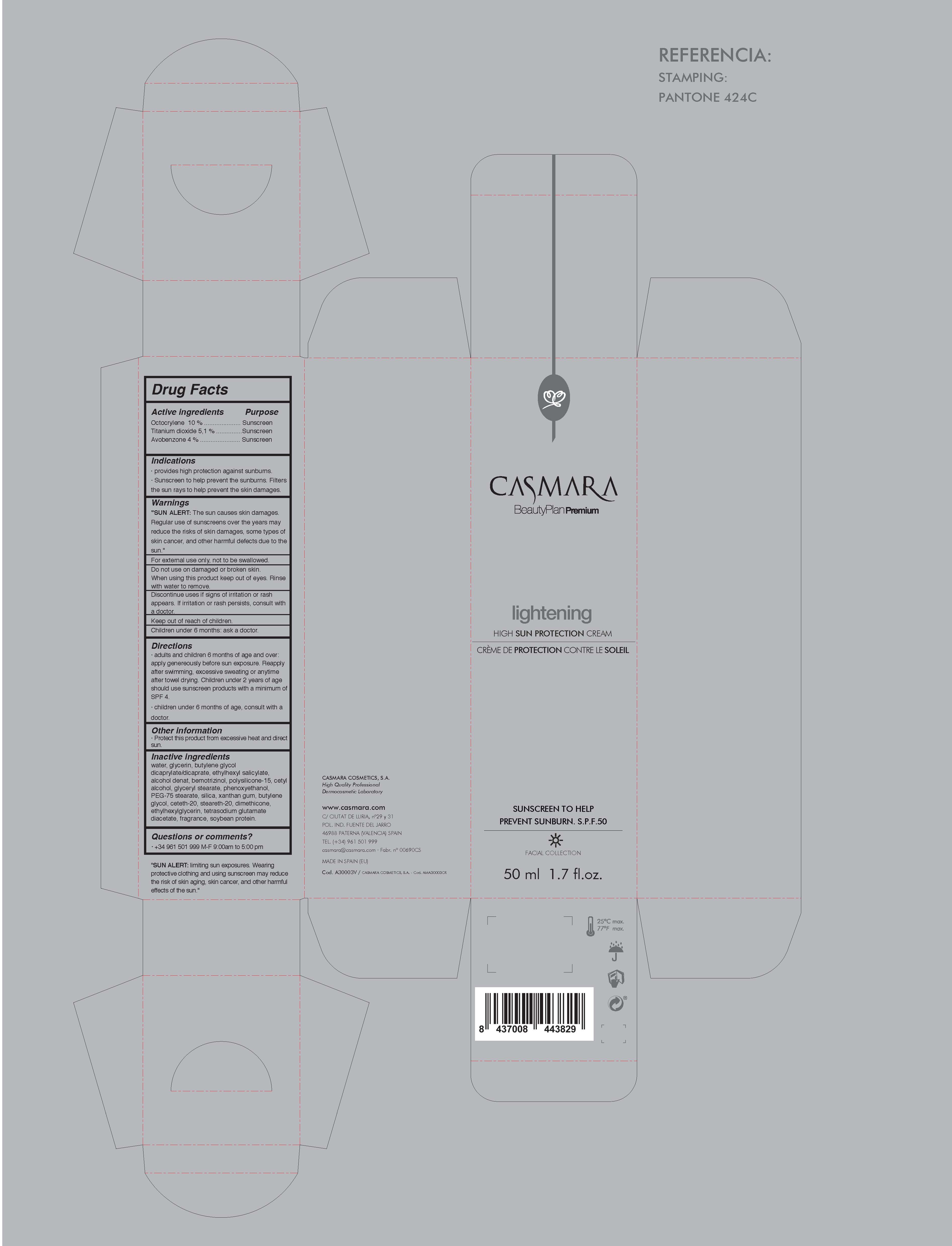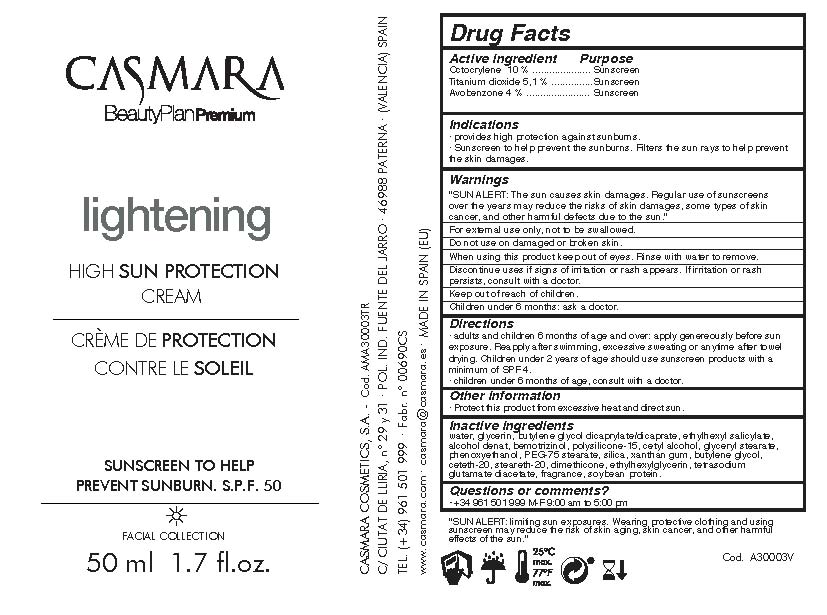 DRUG LABEL: Lightening High Sun Protection Cream
NDC: 20151-105 | Form: CREAM
Manufacturer: Casmara Cosmetics, SA
Category: otc | Type: HUMAN OTC DRUG LABEL
Date: 20170619

ACTIVE INGREDIENTS: TITANIUM DIOXIDE 5.1 mg/1 mL; AVOBENZONE 4 mg/1 mL; OCTOCRYLENE 10 mg/1 mL
INACTIVE INGREDIENTS: DIMETHICONE 0.12 mg/1 mL; SOYBEAN 0.02 mg/1 mL; CETETH-20 0.372 mg/1 mL; STEARETH-20 0.372 mg/1 mL; BUTYLENE GLYCOL 0.5 mg/1 mL; OCTISALATE 5 mg/1 mL; POLYSILICONE-15 3 mg/1 mL; ETHYLHEXYLGLYCERIN 0.1 mg/1 mL; WATER 43.56 mg/1 mL; ALCOHOL 4.8 mg/1 mL; BUTYLENE GLYCOL DICAPRYLATE/DICAPRATE 5 mg/1 mL; TETRASODIUM GLUTAMATE DIACETATE 0.094 mg/1 mL; BEMOTRIZINOL 4 mg/1 mL; GLYCERIN 7 mg/1 mL; CETYL ALCOHOL 1.87 mg/1 mL; GLYCERYL STEARATE SE 1.875 mg/1 mL; PHENOXYETHANOL 0.9 mg/1 mL; PEG-75 STEARATE 0.872 mg/1 mL; SILICON DIOXIDE 0.78 mg/1 mL; XANTHAN GUM 0.6 mg/1 mL

Lightening High Sun Protection Cream

ACTIVE INGREDIENTS PURPOSE

Octocrylene 10%.................... Sunscreen

Titanium Dioxide 5.1%............ Sunscreen

Avobenzone 4%..................... Sunscreen

Warnings

SUN ALERT: The sun causes skin damages. Regular use of sunscreens over the years may reduce the risks of skin damages, some types of skin cancer, and other harmful effects due to the sun

For external use only, not to be swallowed.

Do not use on damaged or broken skin.

When using this product keep our of the eyes. Rinse with water to remove.

DIscontinue uses if signs or irritationsor rash appears. If irritation or rash persists, consult with a doctor.

Keep out of reach of children.

Children under 6 months: as a doctor.

WARNINGS

Stop use and ask a doctor if rash occurs

Children under 6 months: ask a doctor

Warnings

Keep out of reach of children

Questions or comments?

+ 34 961 501 999 M-F 9:00 am to 5:00 pm

Other Information

. keep the product in a cool and dry place

Directions

- adults and childrens 6 months of age and over: apply generaously before sun exposure. Reapply after swiming, excessive sweating or anytime after towel drying. Children under 2 years of age or less should use sunscreen products with a minium of SPF 4
- children under 6 months of age, consult with a doctor

DOSAGE AND ADMINISTRATION

- adults and childrens 6 months of age and over: apply generaously before sun exposure. Reapply after swiming, excessive sweating or anytime after towel drying. Children under 2 years of age or less should use sunscreen products with a minium of SPF 4
- children under 6 months of age, consult with a doctor

Uses

- provides high protection against sunburns
- sunscreen to help prevent sunburns. FIlters the sun rays to help prevent the skin damages

Inactive Ingredients

Water, Glycerin, Butylene glycol dicaprylate/dicaprate, Ethylhexyl salicylate, Alcohol denat, Bemotrizinol, Polysilicone-15, Cetyl alcohol, Glyceryl stearate, Phenoxyethanol, PEG-75 stearate, Silica, Xanthan gum, Butylene glycol, Ceteth-20, Steareth-20, Dimethicone, Ethylhexylglycerin, Tetrasodium glutamate diacetate, Fragrance, Soybean protein

Uses

- provides high protection against sunburns
- sunscreen to help prevent sunburns. FIlters the sun rays to help prevent the skin damages